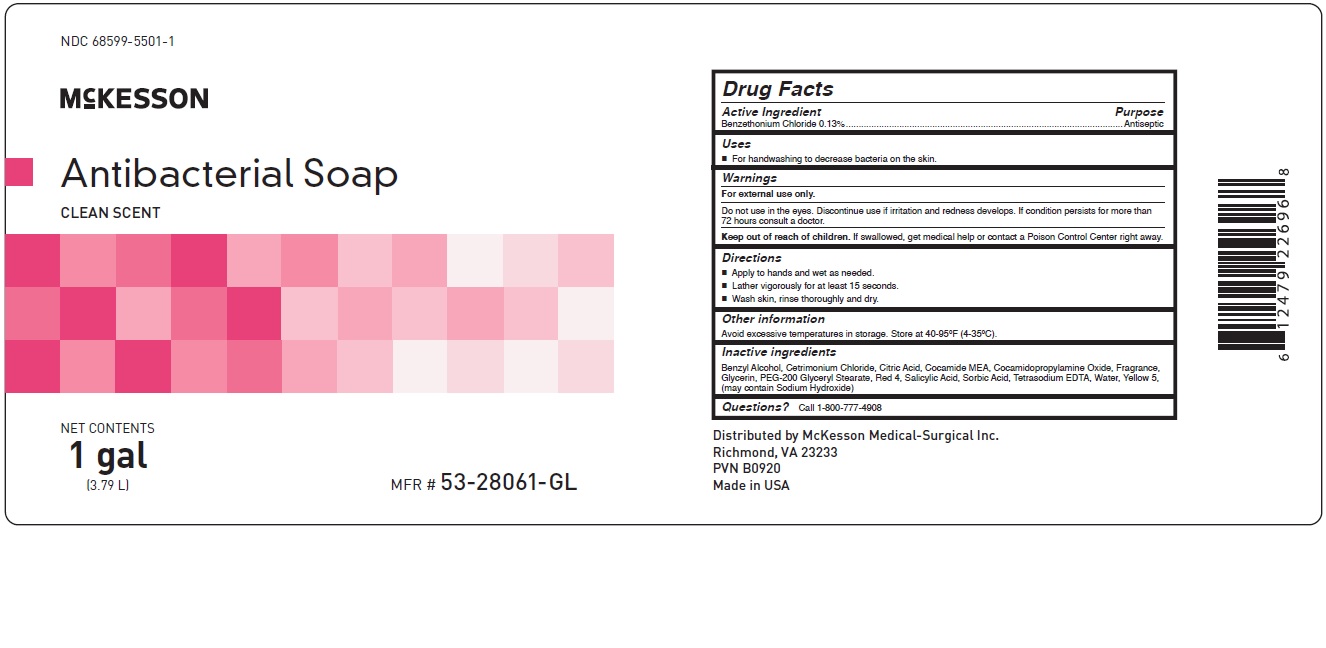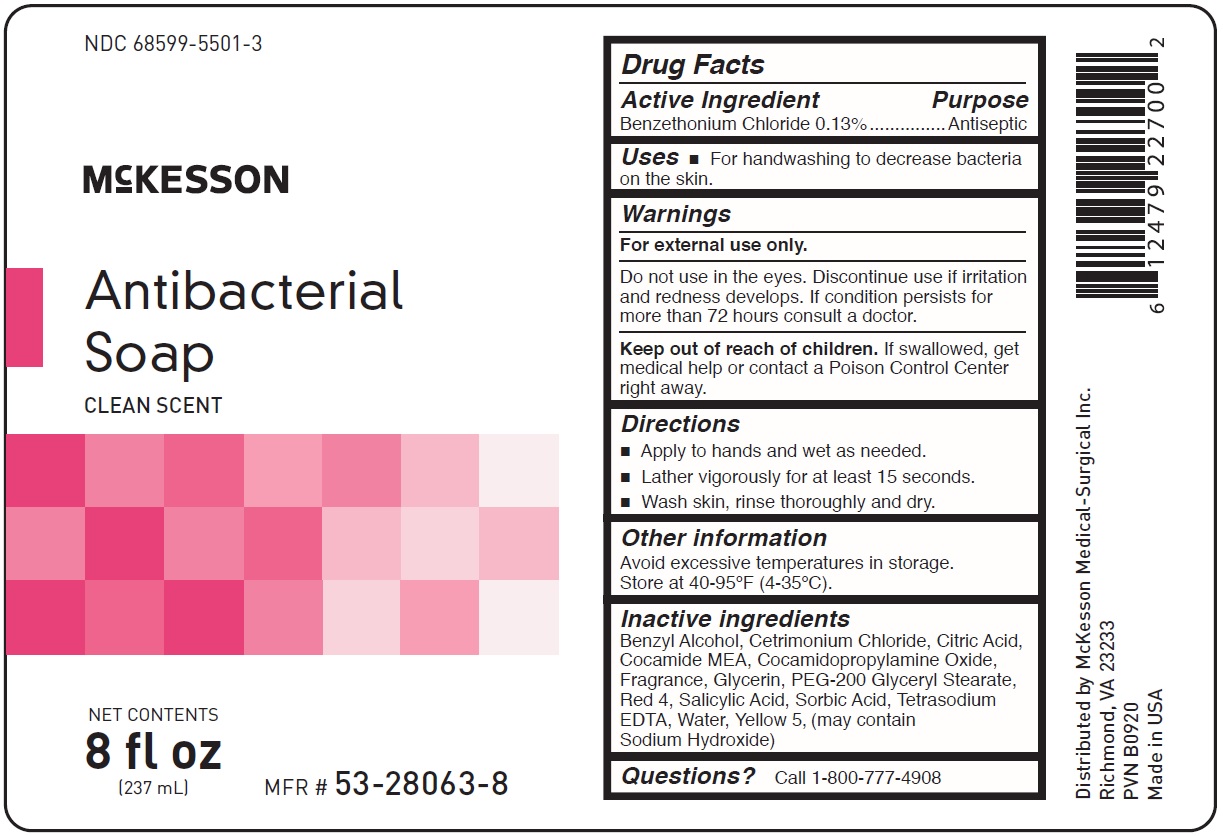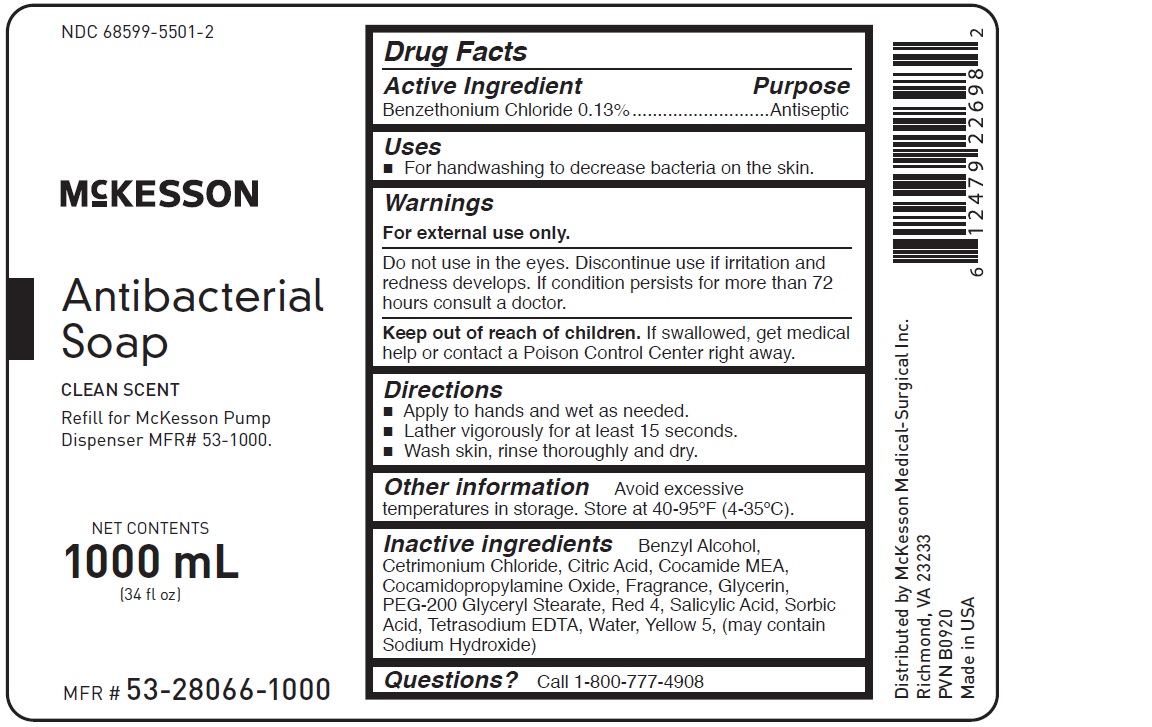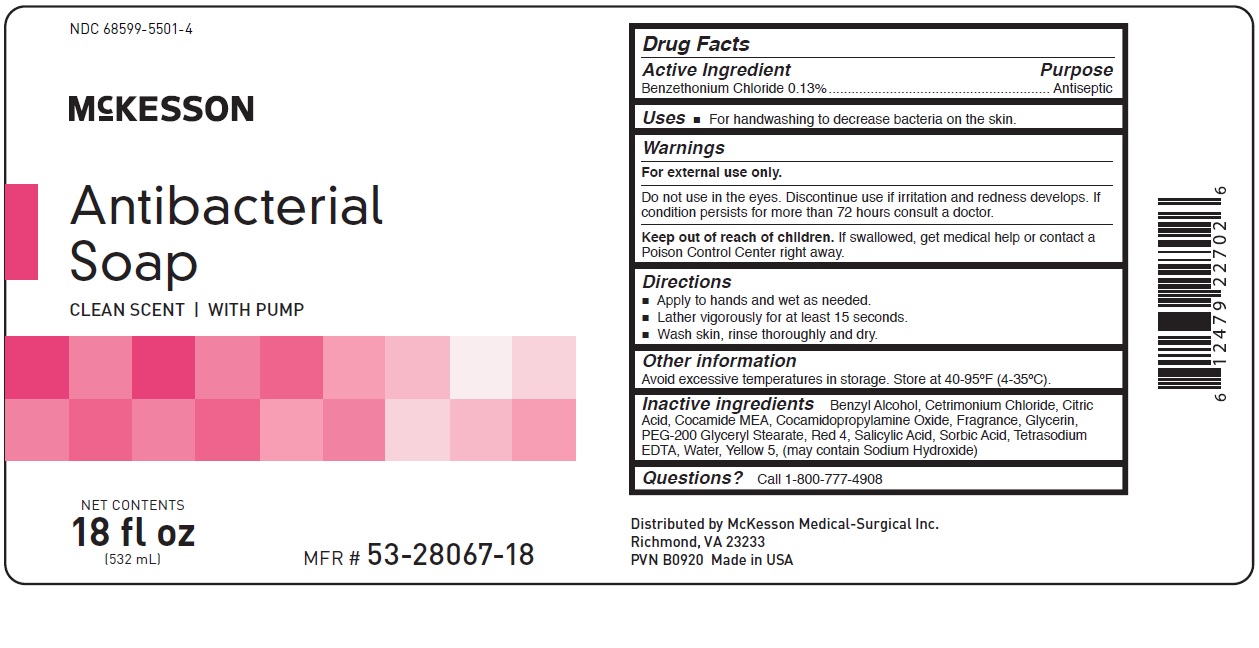 DRUG LABEL: Antibacterial
NDC: 68599-5501 | Form: LIQUID
Manufacturer: McKesson
Category: otc | Type: HUMAN OTC DRUG LABEL
Date: 20241011

ACTIVE INGREDIENTS: BENZETHONIUM CHLORIDE 0.13 g/100 mL
INACTIVE INGREDIENTS: SALICYLIC ACID; SORBIC ACID; EDETATE SODIUM; COCAMIDOPROPYLAMINE OXIDE; PEG-200 GLYCERYL STEARATE; BENZYL ALCOHOL; CITRIC ACID MONOHYDRATE; WATER; COCO MONOETHANOLAMIDE; GLYCERIN; CETRIMONIUM CHLORIDE; FD&C YELLOW NO. 5; FD&C RED NO. 4

McKesson Antibacterial Soap

Drug Facts

Active Ingredient

Benzethonium Chloride @ 0.13%

Purpose

Antiseptic

INDICATIONS AND USAGE

Uses • For handwashing to decrease bacteria on the skin.

Warnings
For external use only .

Do not use in the eyes. Discontinue use if irritation and redness
develops. If condition persists for more than 72 hours consult a
doctor.

Keep out of reach of children. If swallowed, get medical help or contact a Poison Control Center right away.

Directions
• Apply to hands and wet as needed.
• Lather vigorously for at least 15 seconds.
• Wash skin, rinse thoroughly and dry.

Other information- Protect from freezing. Avoid excessive heat.

Inactive Ingredients:
Benzyl Alcohol, Cetrimonium Chloride, Citric Acid, Cocamide MEA, Cocamidopropylamine Oxide, Fragrance,
Glycerin, PEG-200 Glyceryl Stearate, Red 4, Salicylic Acid, Sorbic Acid, Tetrasodium EDTA, Water, Yellow 5,
(may contain Sodium Hydroxide)

General Questions?Call 1-800-777-4908

PACKAGE LABEL

NDC 68599-5501-1
McKesson
Antibacterial Soap
Clean Scent
Net Contents
1 gal
(3.79L)

PACKAGE LABEL

NDC 68599-5501-3
McKesson
Antibacterial Soap
Clean Scent with Pump
Net Contents
8 fl oz
(237 mL)

PACKAGE LABEL

NDC 68599-5501-2
McKesson
Antibacterial Soap
Clean Scent
Refill for McKesson Pump Dispensers MFR#53-1000
Net Contents
1000 mL
(34 fl oz)

PACKAGE LABEL

NDC 68599-5501-4
McKesson
Antibacterial Soap
Clean Scent with Pump
Net Contents
18 fl oz
(532 mL)